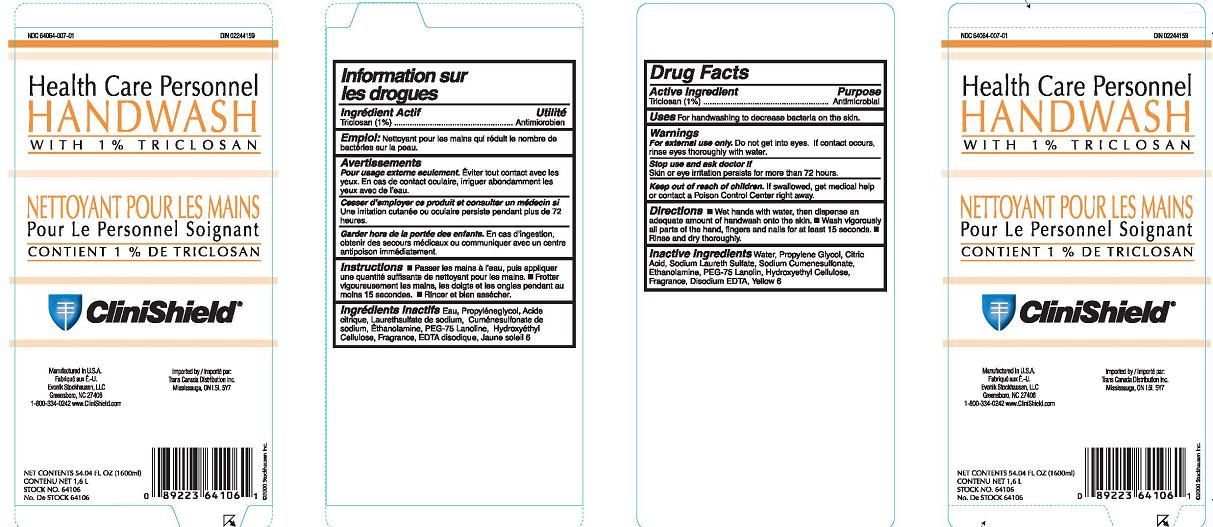 DRUG LABEL: Health Care Personnel Handwash
NDC: 64064-007 | Form: LIQUID
Manufacturer: Evonik Stockhausen, LLC
Category: otc | Type: HUMAN OTC DRUG LABEL
Date: 20110908

ACTIVE INGREDIENTS: Triclosan 1 mL/100 mL
INACTIVE INGREDIENTS: Water; Propylene Glycol; Citric Acid Monohydrate; SODIUM LAURETH SULFATE; Sodium Cumenesulfonate; Monoethanolamine; PEG-75 Lanolin; Edetate Disodium; FD&C Yellow No. 6; HYDROXYETHYL CELLULOSE (2000 CPS AT 1%)

Drug Facts

Active Ingredient

Triclosan (1%)

Purpose

Antimicrobial

Uses

For handwashing to decrease bacteria on the skin.

Warnings

For external use only.

Do not get into eyes. If contact occurs, rinse eyes thoroughly with water.

Stop use and ask doctor if

Skin or eye irritation persists for more than 72 hours

Keep out of reach of children.

If swallowed, get medical help or contact a Poison Control Center right away.

Directions

- Wet hands with water, then dispense an adequate amount of handwash onto the skin.
- Wash vigorously all parts of the hand, fingers and nails for at least15 seconds.
- Rinse and dry thoroughly.

Inactive Ingredients

Water, Propylene Glycol, Citric Acid, Sodium Laureth Sulfate, Sodium cumenesulfonate, Ethanolamine, PEG-75 Lanolin, Hydroxyethyl Cellulose, Fragrance, Disodium EDTA, Yellow 6

Principal Display Panel

NDC 64064-007-01

DIN 02244159

Health Care Personnel

Handwash
With 1% Triclosan

Nettoyant Pour Les Mains

Pour Le Personnel Soignant

Contient 1% de Triclosan

Clinishield

Manufactured in U.S.A.

Fabrique Aux E.-U.

Evonik Stockhausen, LLC

Greensboro, NC 27406

1-800-334-0242 www.CliniShield.com

Imported by/Importe par:

Trans Canada Distribution Inc.

Mississauga, ON L5L 5Y7

Net Contents 54.04 Fl Oz (1600ml)

Contenu Net 1,6 L

Stock No. 64106

No. De Stock 64106